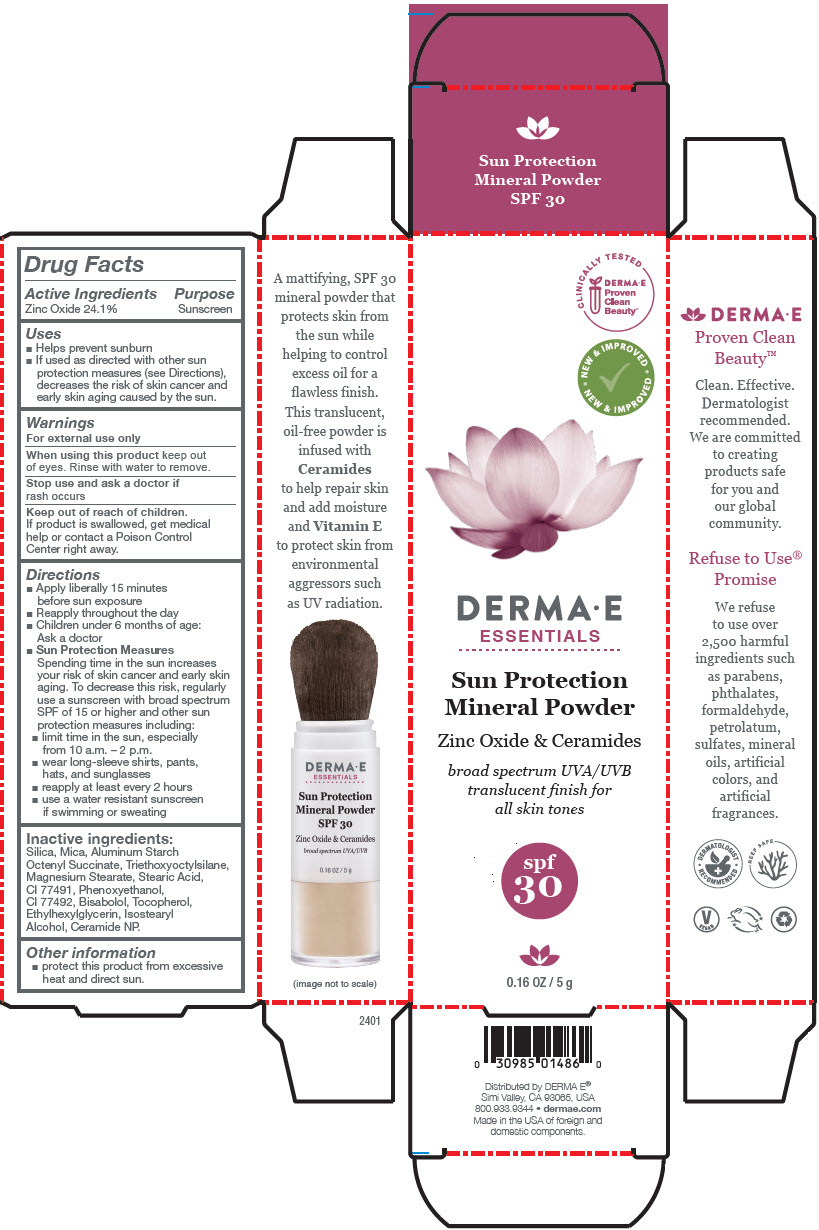 DRUG LABEL: Derma E Sun Protection Mineral 
NDC: 54108-1486 | Form: POWDER
Manufacturer: derma e
Category: otc | Type: HUMAN OTC DRUG LABEL
Date: 20240408

ACTIVE INGREDIENTS: ZINC OXIDE 241 mg/1 g
INACTIVE INGREDIENTS: SILICON DIOXIDE; MICA; ALUMINUM STARCH OCTENYLSUCCINATE; TRIETHOXYCAPRYLYLSILANE; MAGNESIUM STEARATE; STEARIC ACID; FERRIC OXIDE RED; PHENOXYETHANOL; FERRIC OXIDE YELLOW; .ALPHA.-BISABOLOL, (+)-; .ALPHA.-TOCOPHEROL; ETHYLHEXYLGLYCERIN; ISOSTEARYL ALCOHOL; CERAMIDE NP

DERMA E Sun Protection Mineral
SPF 30

Drug Facts

Active Ingredients

Zinc Oxide 24.1%

Purpose

Sunscreen

Uses

- Helps prevent sunburn
- If used as directed with other sun protection measures (see Directions), decreases the risk of skin cancer and early skin aging caused by the sun.

Warnings

For external use only

When using this product keep out of eyes. Rinse with water to remove.

Stop use and ask a doctor if rash occurs

Keep out of reach of children.

If product is swallowed, get medical help or contact a Poison Control Center right away.

Directions

- Apply liberally 15 minutes before sun exposure
- Reapply throughout the day
- Children under 6 months of age: Ask a doctor
- Sun Protection Measures
  Spending time in the sun increases your risk of skin cancer and early skin aging. To decrease this risk, regularly use a sunscreen with broad spectrum SPF of 15 or higher and other sun protection measures including:
  - limit time in the sun, especially from 10 a.m. – 2 p.m.
  - wear long-sleeve shirts, pants, hats, and sunglasses
  - reapply at least every 2 hours
  - use a water resistant sunscreen if swimming or sweating

Inactive ingredients

Silica, Mica, Aluminum Starch Octenyl Succinate, Triethoxyoctylsilane, Magnesium Stearate, Stearic Acid, CI 77491, Phenoxyethanol, CI 77492, Bisabolol, Tocopherol, Ethylhexylglycerin, Isostearyl Alcohol, Ceramide NP.

Other information

- protect this product from excessive heat and direct sun.

Distributed by DERMA E®
Simi Valley, CA 93065, USA

PRINCIPAL DISPLAY PANEL - 5 g Bottle Box

CLINICALLY TESTED

DERMA • E
Proven
Clean
Beauty™

• NEW & IMPROVED
NEW & IMPROVED •

DERMA • E
ESSENTIALS

Sun Protection
Mineral Powder

Zinc Oxide & Ceramides

broad spectrum UVA/UVB
translucent finish for
all skin tones

spf
30

0.16 OZ / 5 g